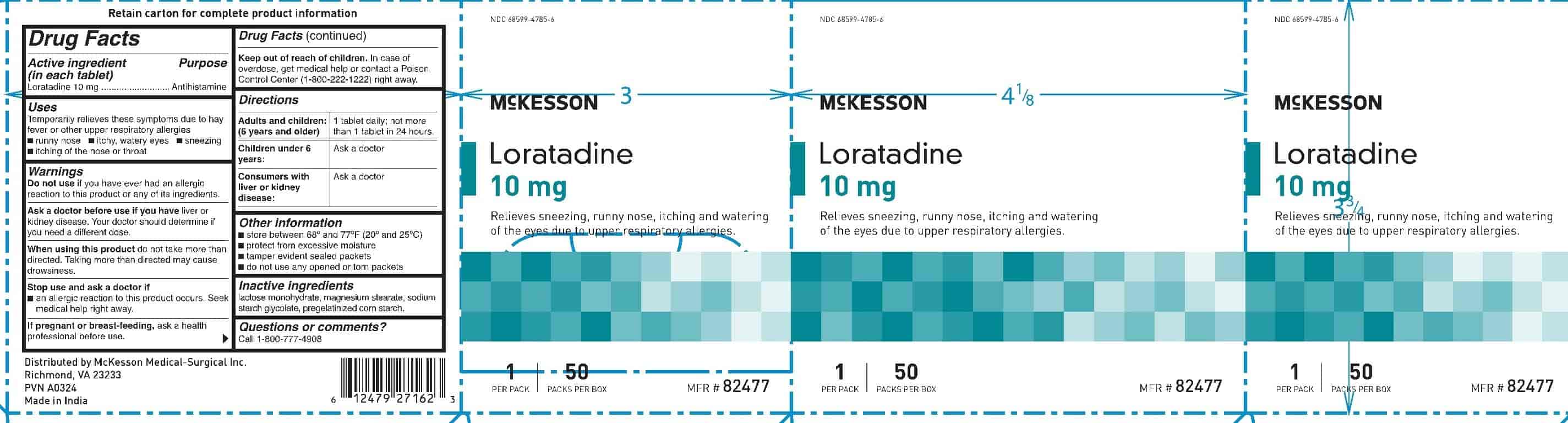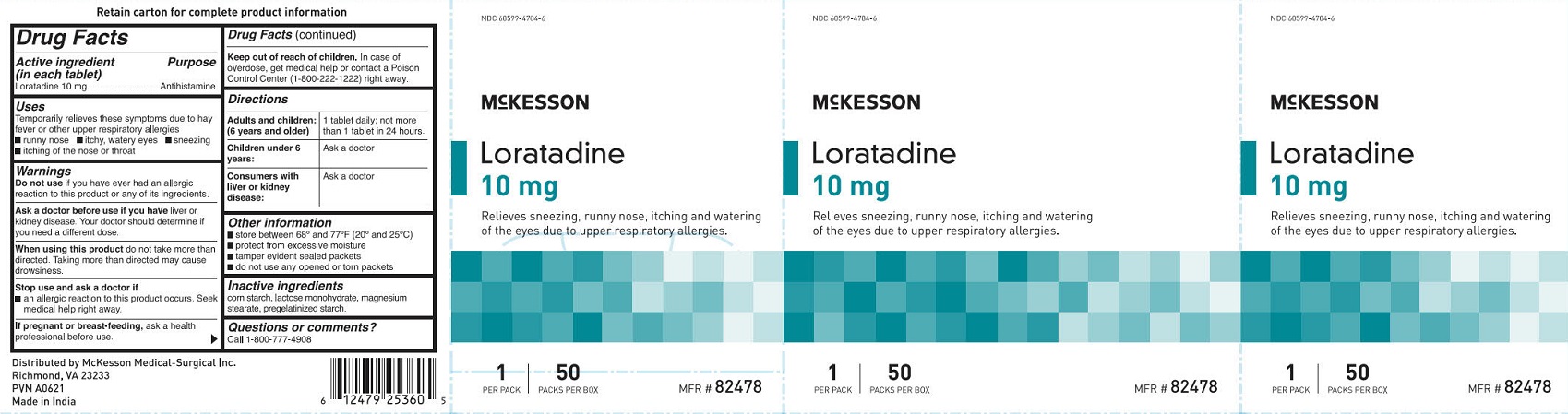 DRUG LABEL: McKesson Loradatine
NDC: 68599-4785 | Form: TABLET
Manufacturer: McKesson Medical Surgical
Category: otc | Type: HUMAN OTC DRUG LABEL
Date: 20251023

ACTIVE INGREDIENTS: LORATADINE 10 mg/1 1
INACTIVE INGREDIENTS: MAGNESIUM STEARATE; WATER; LACTOSE MONOHYDRATE; STARCH, CORN; SODIUM STARCH GLYCOLATE TYPE A POTATO

McKesson Loratadine 10 mg

Drug Facts

Active ingredient (in each tablet)

Loratadine 10 mg

Purpose

Antihistamine

Uses

Temporarily relieves these symptoms due to hay fever or other upper respiratory allergies

- runny nose
- itchy, watery eyes
- sneezing
- itching of the nose or throat

Warnings

Do not use if you have ever had an allergic reaction to this product or any of its ingredients.

Ask a doctor before use if you have liver or kidney disease.

Your doctor should determine if you need a different dose.

When using this product do not take more than directed.

Taking more than directed may cause drowsiness.

Stop use and ask a doctor if

- an allergic reaction to this product occurs. Seek medical help right away.

PREGNANCY OR BREAST FEEDING

If pregnant or breast-feeding, ask a health professional before use.

Keep out of reach of children.

In case of overdose, get medical help or contact a Poison Control Center (1-800-222-1222) right away.

Directions

Adults and children (6 years and older): 1 tablet daily; not more than 1 tablet in 24 hours.

Children under 6 years: Ask a doctor

Consumers with liver or kidney disease: Ask a doctor

Other information

- store between 68º and 77ºF (20º and 25ºC)
- protect from excessive moisture
- tamper evident sealed packets
- do not use any opened or torn packets

Inactive ingredients

lactose monohydrate, magnesium stearate, sodium starch glycolate, pregelatinized starch.

Questions or comments?

Call 1-800-777-4908

PACKAGE LABEL

NDC 68599-4784-6

McKesson

Loratadine 10 mg

Relieves sneezing, runny nose, itching and watering of the eyes due to upper respiratory allergies.

1 per Pack

50 Packs Per Box

MFR # 82478

PACKAGE LABEL

NDC 68599-4785-6

McKesson

Loratadine

10 mg

Removes sneezing, runny nose,itching and watering

of the eyes due to upper respiratory allergies

1 | 50

PER PACK PACKS PER BOX MFR # 82477